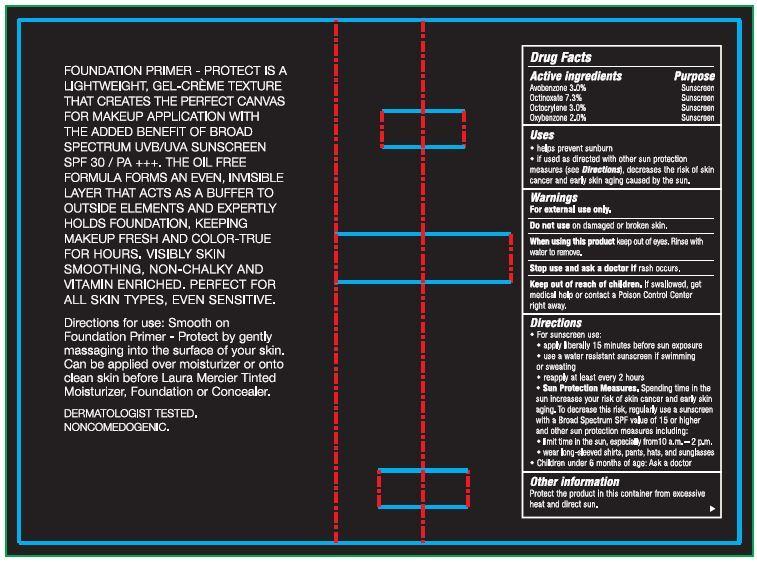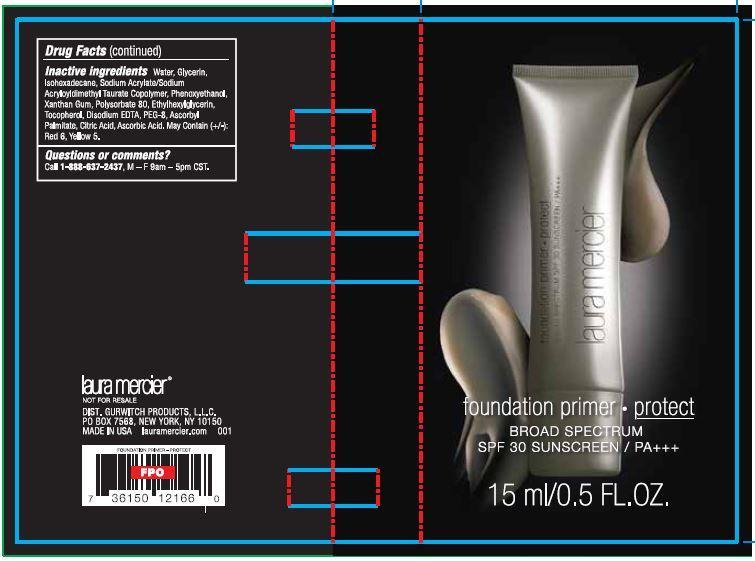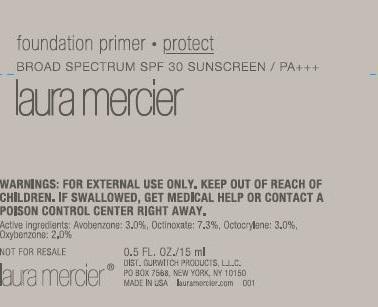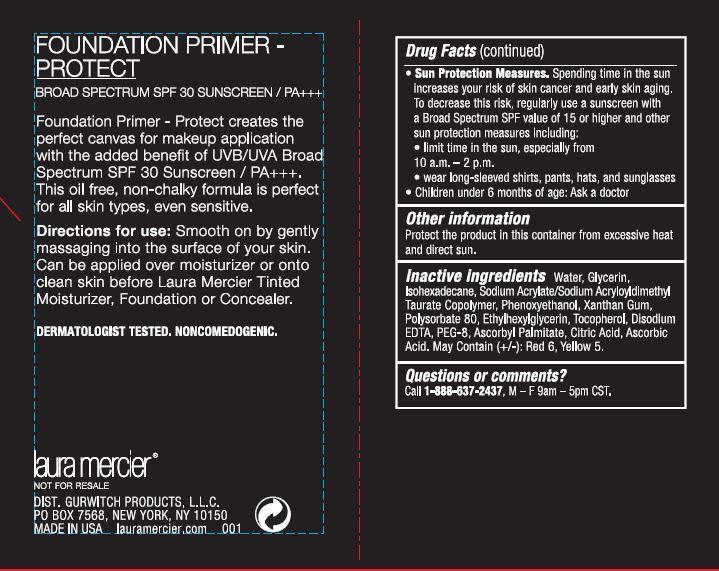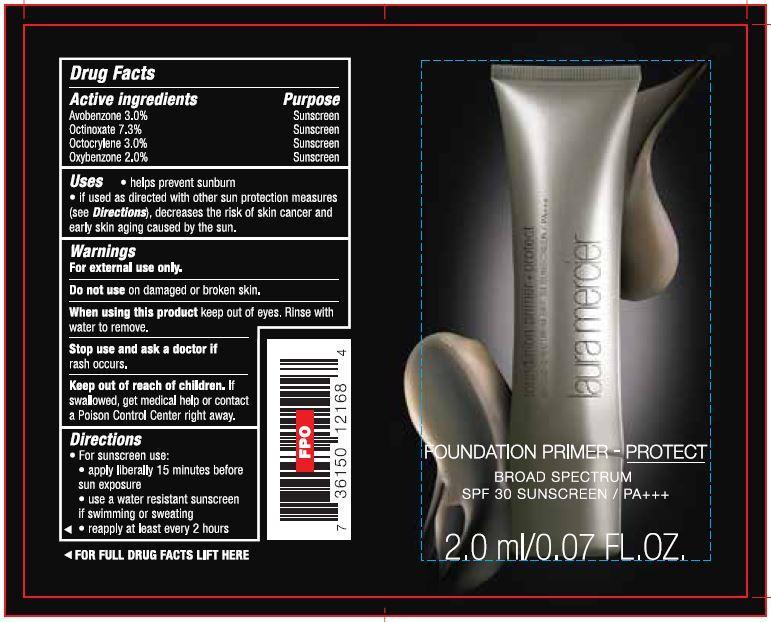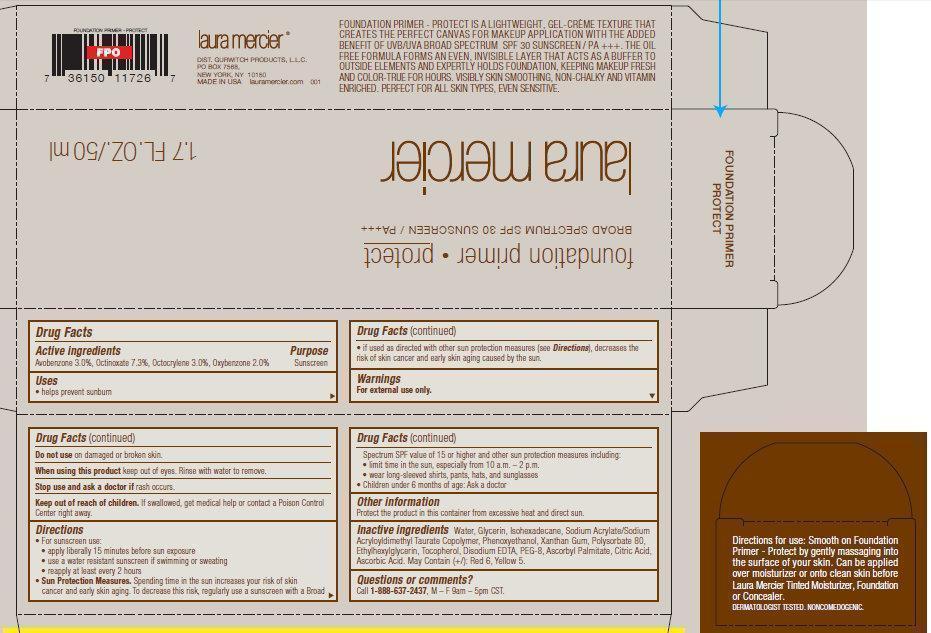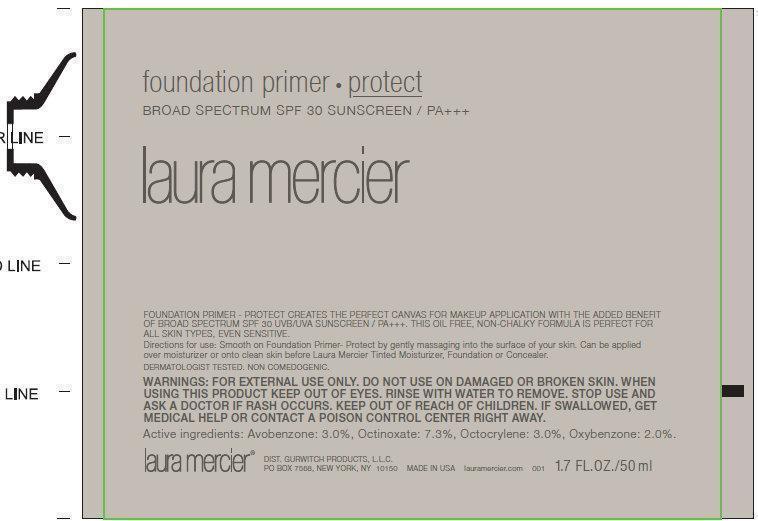 DRUG LABEL: Laura Mercier Foundation Primer Protect
NDC: 65342-7005 | Form: LOTION
Manufacturer: Gurwitch Products, LLC
Category: otc | Type: HUMAN OTC DRUG LABEL
Date: 20140415

ACTIVE INGREDIENTS: AVOBENZONE 30 mg/1 mL; OCTINOXATE 73 mg/1 mL; OCTOCRYLENE 30 mg/1 mL; OXYBENZONE 20 mg/1 mL
INACTIVE INGREDIENTS: WATER; GLYCERIN; ISOHEXADECANE; PHENOXYETHANOL; XANTHAN GUM; POLYSORBATE 80; ETHYLHEXYLGLYCERIN; TOCOPHEROL; EDETATE DISODIUM; POLYETHYLENE GLYCOL 400; ASCORBYL PALMITATE; CITRIC ACID MONOHYDRATE; ASCORBIC ACID; D&C RED NO. 6; FD&C YELLOW NO. 5

Laura Mercier Foundation Primer Protect SPF 30

Active ingredients

Avobenzone 3.0%, Octinoxate 7.3%, Octocrylene 3.0%, Oxybenzone 2.0%

Purpose

Sunscreen

Uses

- helps prevent sunburn
- if used as directed with other sun protection measures (see Directions), decreases the risk of skin cancer and early skin aging caused by the sun.

Warnings

For external use only.

Do not use

on damaged or broken skin.

When using this product

keep out of eyes. Rinse with water to remove.

Stop use and ask a doctor if

rash occurs.

Keep out of reach of children.

If swallowed, get medical help or contact a Poison Control Center right away.

Directions

- For sunscreen use:
- apply liberally 15 minutes before sun exposure
- use a water resistant sunscreen if swimming or sweating
- reapply at least ever y 2 hours
- Sun Protection Measures. Spending time in the sun increases your risk of skin cancer and early skin aging. To decrease this risk, regularly use a sunscreen with a Broad Spectrum SPF value of 15 or higher and other sun protection mea sures including:
- limit time in the sun, especially from 10 a.m. – 2 p.m.
- wear long-sleeved shirts, pants, hats, and sunglasses
- Children under 6 months of age: Ask a doctor

Other information

Protect the product in this container from excessive heat and direct sun.

Inactive ingredients

Water, Glycerin, Isohexadecane, Sodium Acrylate/Sodium Acryloyldimethyl Taurate Copolymer, Phenoxyethanol, Xanthan Gum, Polysorbate 80, Ethylhexylglycerin, Tocopherol, Disodium EDTA, PEG-8, Ascorbyl Palmitate, Citric Acid, Ascorbic Acid. May Contain (+/): Red 6, Yellow 5.

Questions or comments?

Call 1-888-637-2437, M – F 9am – 5pm CST .

FOUNDATION PRIMER - PROTECT IS A LIGHTWEIGHT, GEL-CREME TEXTURE THAT CREATES THE PERFECT CANVAS FOR MAKEUP APPLICATION WITH THE ADDED BENEFIT OF UVB/UVA BROAD SPECTRUM SPF 30 SUNSCREEN / PA +++. THE OIL FREE FORMULA FORMS AN EVEN, INVISIBLE LAYER THAT ACTS AS A BUFFER TO OUTSIDE ELEMENTS AND EXPERTLY HOLDS FOUNDATION, KEEPING MAKEUP FRESH AND COLOR-TRUE FOR HOURS. VISIBLY SKIN SMOOTHING, NON-CHALKY AND VITAMIN ENRICHED. PERFECT FOR ALL SKIN TYPES, EVEN SENSITIVE.

laura mercier DIST. GURWITCH PRODUCTS, L.L.C. PO BOX 7568, NEW YORK, NY 10150 MADE IN USA lauramercier.com 001 FOUNDATION PRIMER - PROTECT FPO 7 36150 11726 7

Directions for use: Smooth on Foundation Primer - Protect by gently massaging into the surface of your skin. Can be applied over moisturizer or onto clean skin before Laura Mercier Tinted Moisturizer, Foundation or Concealer. DERMATOLOGIST TESTED. NONCOMEDOGENIC.

FOUNDATION PRIMER - PROTECT FPO 7 36150 12021 2 002

Directions for use: Smooth on Foundation Primer - Protect by gently massaging into the surface of your skin. Can be applied over moisturizer or onto clean skin before Laura Mercier Tinted Moisturizer, Foundation or Concealer.

DERMATOLOGIST TESTED. NONCOMEDOGENIC.

Warnings: For external use only. Avoid contact with eyes. Discontinue use if signs of rash or irritation appear. If irritation persists, consult a doctor.

PACKAGE LABEL

foundation primer - protect BROAD SPECTRUM SPF 30 SUNSCREEN / PA+++

laura mercier 1.7 FL.OZ./50 ml